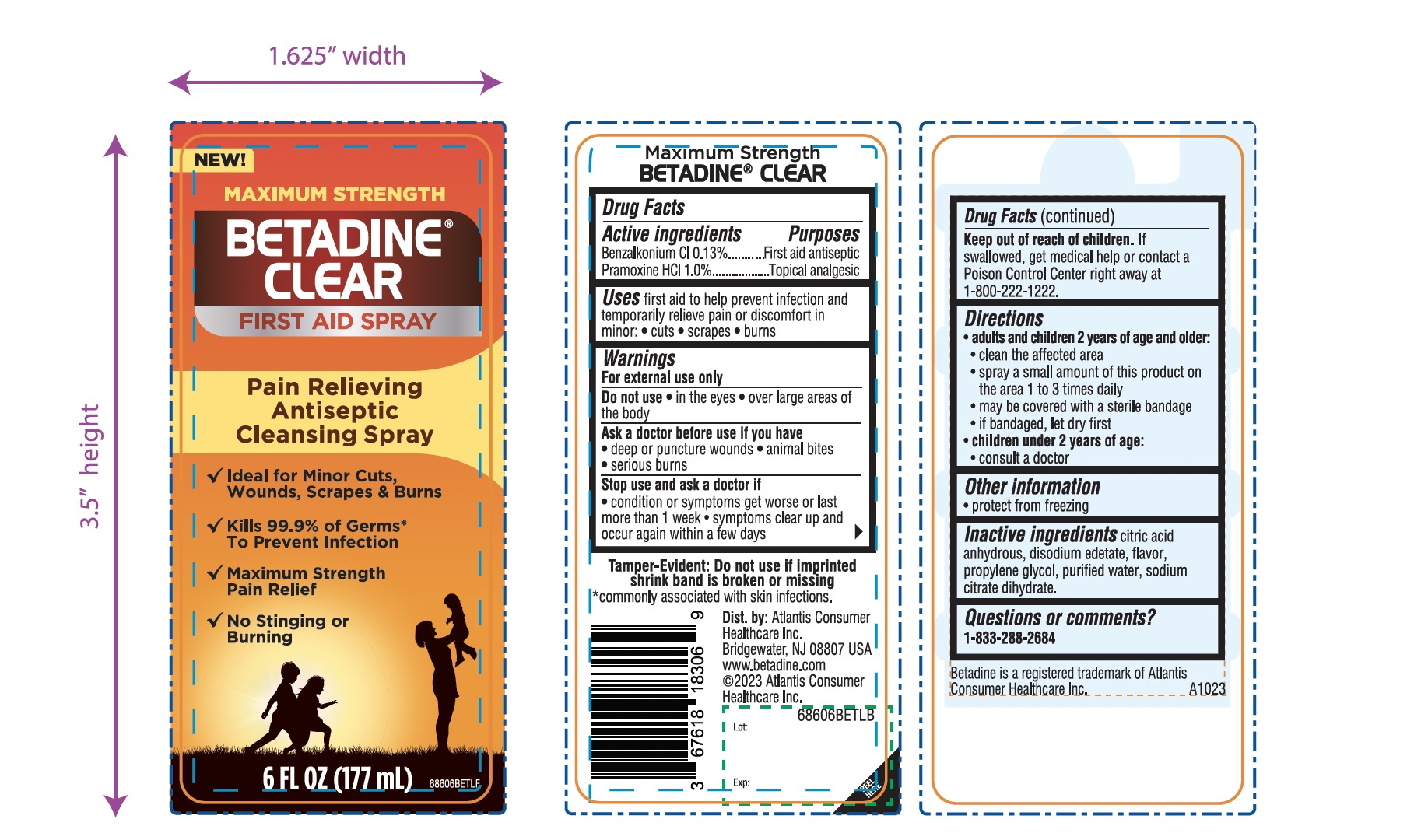 DRUG LABEL: Maximum Strength Betadine Clear
NDC: 67618-183 | Form: SPRAY
Manufacturer: Atlantis Consumer Healthcare, Inc.
Category: otc | Type: HUMAN OTC DRUG LABEL
Date: 20250718

ACTIVE INGREDIENTS: BENZALKONIUM CHLORIDE 0.13 mg/1 mL; PRAMOXINE HYDROCHLORIDE 1 mg/1 mL
INACTIVE INGREDIENTS: ANHYDROUS CITRIC ACID; EDETATE DISODIUM; PROPYLENE GLYCOL; WATER; TRISODIUM CITRATE DIHYDRATE

MAXIMUM STRENGTH BETADINE CLEAR SPRAY

Drug Facts

Active ingredients

Benzalkonium Cl 0.13%

Pramoxine HCl 1.0%

Purpose

First aid Antiseptic

Topical analgesic

Uses

First aid to help prevent infection and relieve pain or discomfort in minor

- cuts
- scrapes
- burns

Warnings

For external use only

Do not use

- in the eyes
- over large areas of the body

Ask a doctor before use if you have

- deep or puncture wounds
- serious burns
- animal bites

Stop use and ask a doctor if

- condition or symptoms get worse or last more than 1 week
- Symptoms clear up and occur again within a few days

Keep out of reach of children.If swallowed, get medical help or contact a Poison Control Center right away at 1-800-222-1222.

Directions

- adults and children 2 years of age and older:
- clean the affected area
- spray a small amount of this product on the area 1 to 3 times daily
- may be covered with sterile bandage
- if bandaged, let dry first
- children under 2 years of age:
- consult a doctor

Other information

- protect from freezing

Inactive ingredients

citric acid anhydrous, disodium edetate, flavor, propylene glycol, purified water, sodium citrate dihydrate.

PACKAGE LABEL

Principal Display Panel

MAXIMUM STRENGTH

BETADINE® CLEAR

FIRST AID SPRAY

Pain Relieving

Antiseptic

Cleansing spray

- Ideal for Minor Cuts, wounds, scrapes & Burns
- Kills 99.9% of Germs* To prevent Infection
- Maximum Strength Pain Relief
- No Stinging or Burning

6 FL OZ (177 mL)

Dist. by: Atlantis Consumer Healthcare Inc.

Bridgewater, NJ 08807 USA

www.betadine.com

©2023 Atlantis Consumer Healthcare Inc.

*commonly associated with skin infections.

Tamper-Evident: Do not use if imprinted shrink band is broken or missing.

Betadine is a registered trademark of Atlantis Consumer Healthcare Inc.